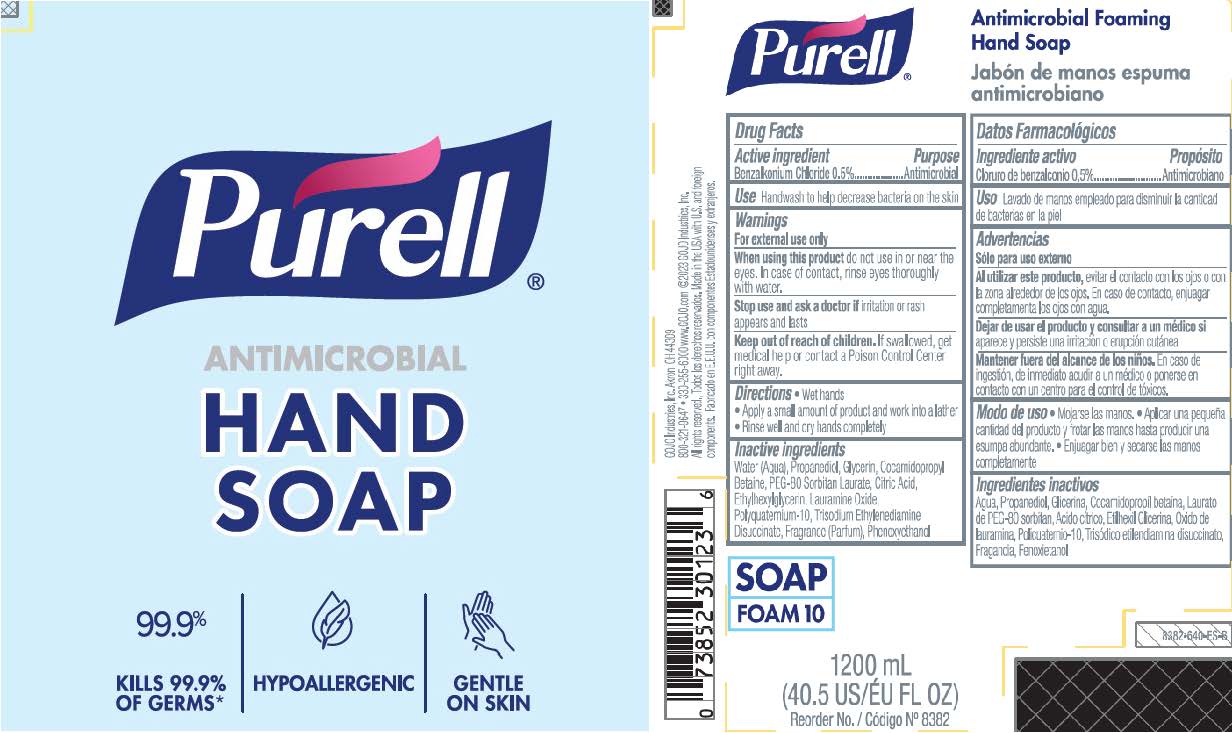 DRUG LABEL: PURELL Antimicrobial Foaming Hand
NDC: 21749-610 | Form: LIQUID
Manufacturer: GOJO Industries, Inc.
Category: otc | Type: HUMAN OTC DRUG LABEL
Date: 20241231

ACTIVE INGREDIENTS: BENZALKONIUM CHLORIDE 0.5 mg/100 mL
INACTIVE INGREDIENTS: WATER; PROPANEDIOL; GLYCERIN; COCAMIDOPROPYL BETAINE; PEG-80 SORBITAN LAURATE; CITRIC ACID MONOHYDRATE; ETHYLHEXYLGLYCERIN; LAURAMINE OXIDE; POLYQUATERNIUM-10 (10000 MPA.S AT 2%); TRISODIUM ETHYLENEDIAMINE DISUCCINATE; PHENOXYETHANOL

PURELL® Antimicrobial Foaming Hand Soap

Active ingredient

Benzalkonium Chloride 0.5%

Purpose

Antimicrobial

Use

• Handwash to help decrease bacteria on the skin

Warnings

For external use only

When using this product do not use in or near the eyes. In case of contact, rinse eyes thoroughly with water.

Stop use and ask a doctor if irritation or rash appears and lasts

Keep out of reach of children. If swallowed, get medical help or contact a Poison Control Center right away.

Directions

• Wet hands

• Apply a small amount of product and work into a lather

• Rinse well and dry hands completely

Inactive Ingredients

Water (Aqua), Propanediol, Glycerin, Cocamidopropyl Betaine, PEG-80 Sorbitan Laurate, Citric Acid, Ethylhexylglycerin, Lauramine Oxide, Polyquaternium-10, Trisodium Ethylenediamine Disuccinate, Fragrance (Parfum), Phenoxyethanol